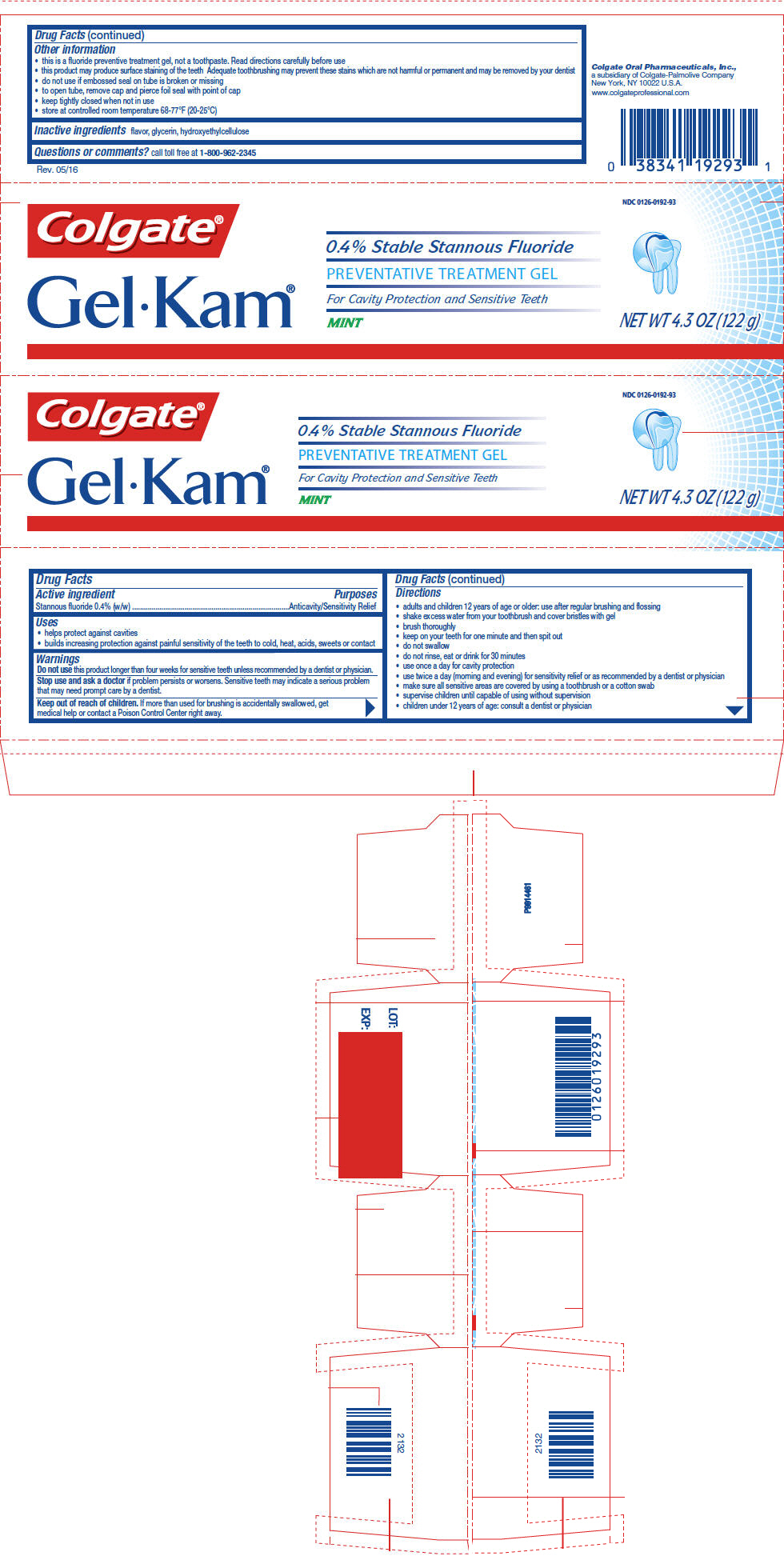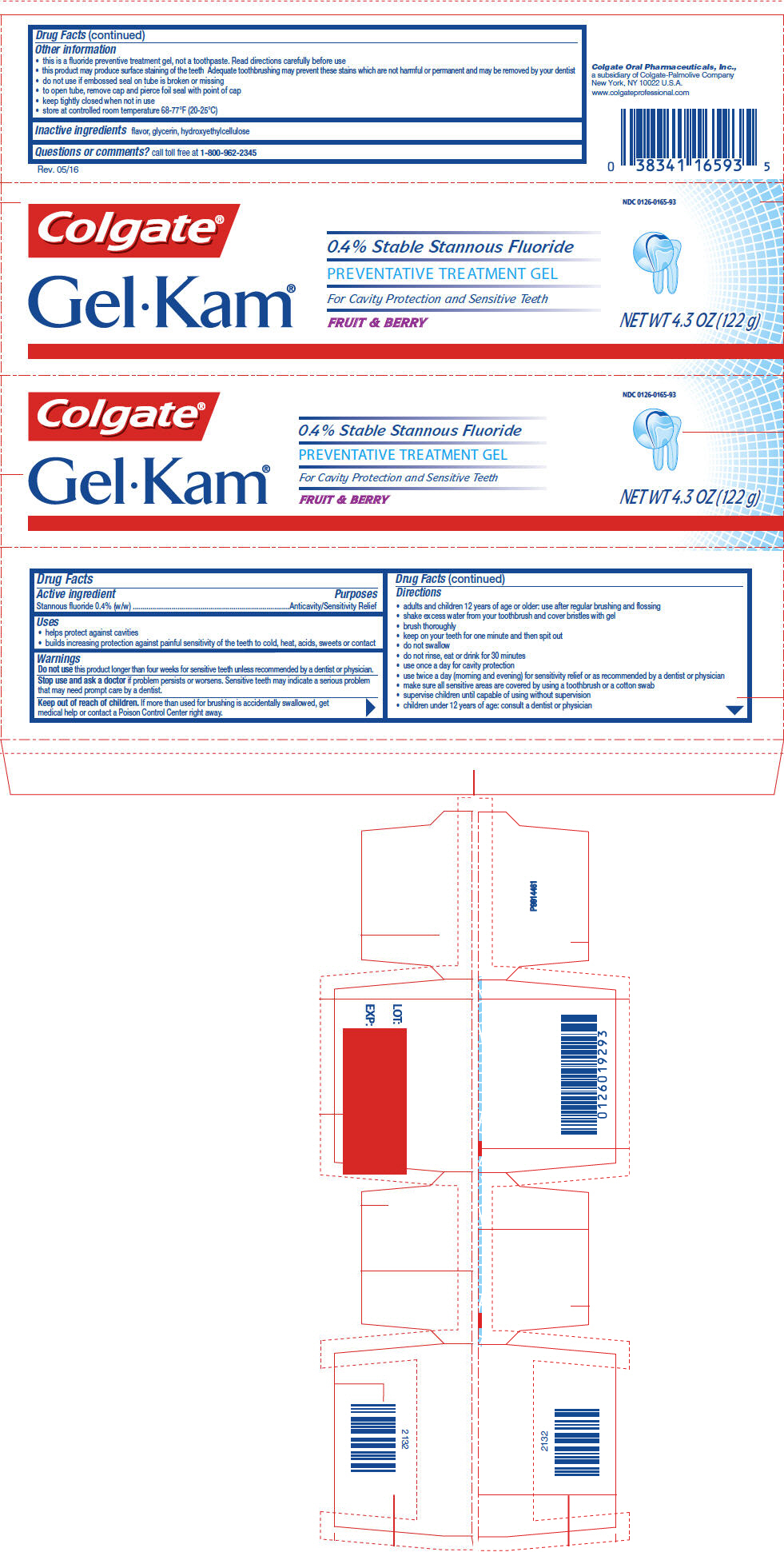 DRUG LABEL: Gel-Kam Mint
NDC: 0126-0192 | Form: GEL, DENTIFRICE
Manufacturer: Colgate Oral Pharmaceuticals, Inc.
Category: otc | Type: HUMAN OTC DRUG LABEL
Date: 20240118

ACTIVE INGREDIENTS: STANNOUS FLUORIDE 1 mg/1 g
INACTIVE INGREDIENTS: GLYCERIN; HYDROXYETHYL CELLULOSE, UNSPECIFIED

Gel-Kam®

Drug Facts

Active ingredient

Stannous fluoride 0.4% (w/w)

Purposes

Anticavity/Sensitivity Relief

Uses

- helps protect against cavities
- builds increasing protection against painful sensitivity of the teeth to cold, heat, acids, sweets or contact

Warnings

Do not use this product longer than four weeks for sensitive teeth unless recommended by a dentist or physician.

Stop use and ask a doctor if problem persists or worsens. Sensitive teeth may indicate a serious problem that may need prompt care by a dentist.

Keep out of reach of children. If more than used for brushing is accidentally swallowed, get medical help or contact a Poison Control Center right away.

Directions

- adults and children 12 years of age or older: use after regular brushing and flossing
- shake excess water from your toothbrush and cover bristles with gel
- brush thoroughly
- keep on your teeth for one minute and then spit out
- do not swallow
- do not rinse, eat or drink for 30 minutes
- use once a day for cavity protection
- use twice a day (morning and evening) for sensitivity relief or as recommended by a dentist or physician
- make sure all sensitive areas are covered by using a toothbrush or a cotton swab
- supervise children until capable of using without supervision
- children under 12 years of age: consult a dentist or physician

Other information

- this is a fluoride preventive treatment gel, not a toothpaste. Read directions carefully before use
- this product may produce surface staining of the teeth Adequate toothbrushing may prevent these stains which are not harmful or permanent and may be removed by your dentist
- do not use if embossed seal on tube is broken or missing
- to open tube, remove cap and pierce foil seal with point of cap
- keep tightly closed when not in use
- store at controlled room temperature 68-77°F (20-25°C)

Inactive ingredients

flavor, glycerin, hydroxyethylcellulose

Questions or comments?

call toll free at 1-800-962-2345

PRINCIPAL DISPLAY PANEL - 122 g Tube Carton - Mint

NDC 0126-0192-93

Colgate®

Gel•Kam®

0.4% Stable Stannous Fluoride
PREVENTATIVE TREATMENT GEL
For Cavity Protection and Sensitive Teeth
MINT

NET WT 4.3 OZ (122 g)

PRINCIPAL DISPLAY PANEL - 122 g Tube Carton - Fruit and Berry

NDC 0126-0165-93

Colgate®

Gel•Kam®

0.4% Stable Stannous Fluoride
PREVENTATIVE TREATMENT GEL
For Cavity Protection and Sensitive Teeth
FRUIT & BERRY

NET WT 4.3 OZ (122 g)